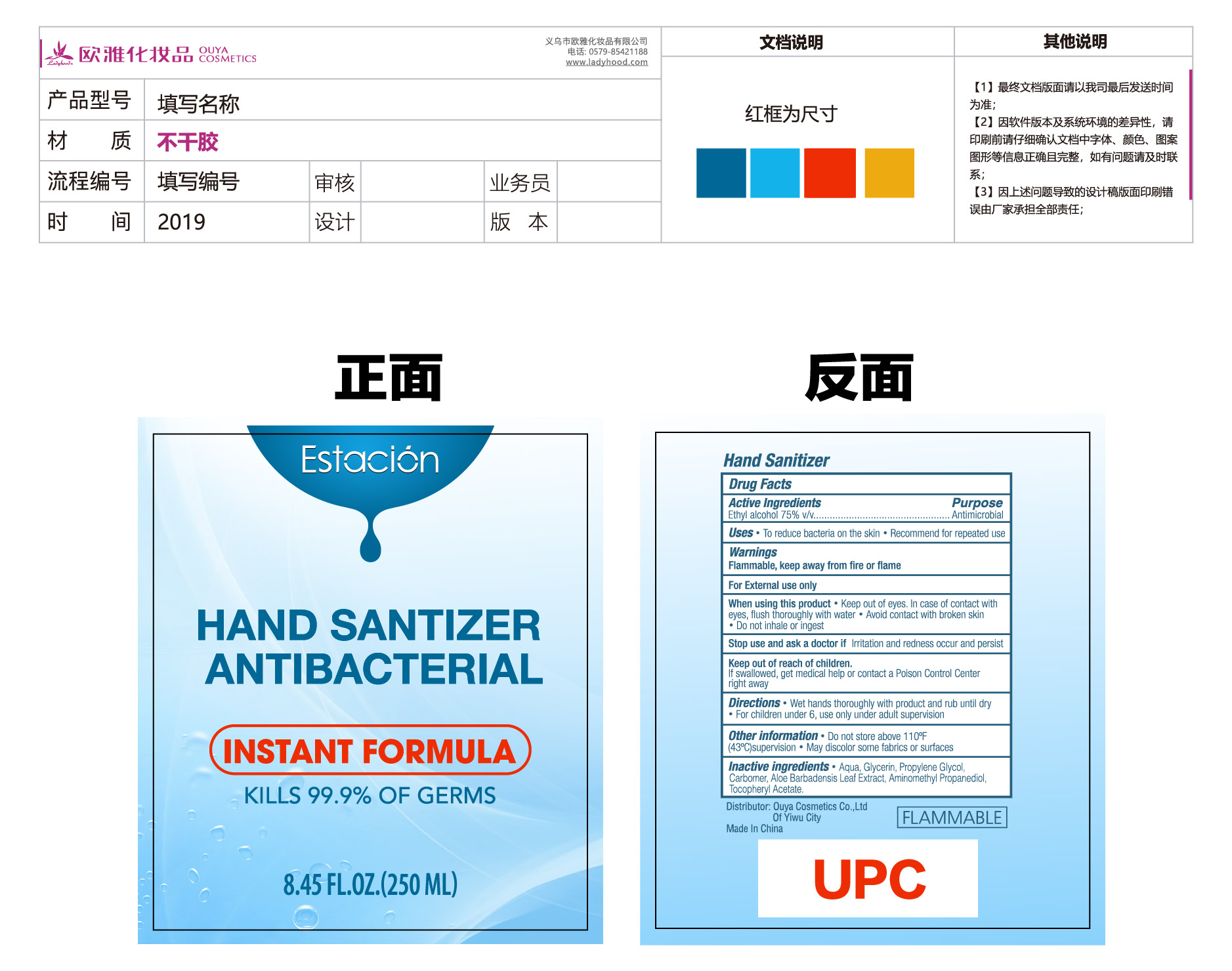 DRUG LABEL: ESTACION  HAND SANITIZER ANTIBACTERIAL
NDC: 54699-001 | Form: SOLUTION
Manufacturer: Ouya Cosmetics Co., Ltd of Yiwu
Category: otc | Type: HUMAN OTC DRUG LABEL
Date: 20200427

ACTIVE INGREDIENTS: ALCOHOL 75 mL/100 mL
INACTIVE INGREDIENTS: GLYCERIN; PROPYLENE GLYCOL; WATER; CARBOMER 934; AMINOMETHYL PROPANEDIOL; ALPHA-TOCOPHEROL ACETATE

NA

Active Ingredient(s)

Ethyl Alcohol 75% v/v. Purpose: Antiseptic

Purpose

Antimicrobial

Use

To reduce bacteria on the skin

Recommended for repeated use

Warnings

Flammable. Keep away from fire or flame

For external use only.

When using this product keep out of eyes. In case of contact with eyes, flush thoroughly with water.

Avoid contact with broken skin

Do not inhale or ingest

Stop use and ask a doctor if irritation or redness occur and persist

Keep out of reach of children. If swallowed, get medical help or contact a Poison Control Center right away.

Directions

- Wet hands thoroughly with product and rub until dry
- For children under 6, use only under adult supervision

Other information

Do not store above 110F (43C)

May discolor some fabrics or surfaces

Inactive ingredients

Water, propylene glycol, glycerin, carbomer, aloe barbadensis leaf extract, aminomethyl propanediol, tocopheryl acetate